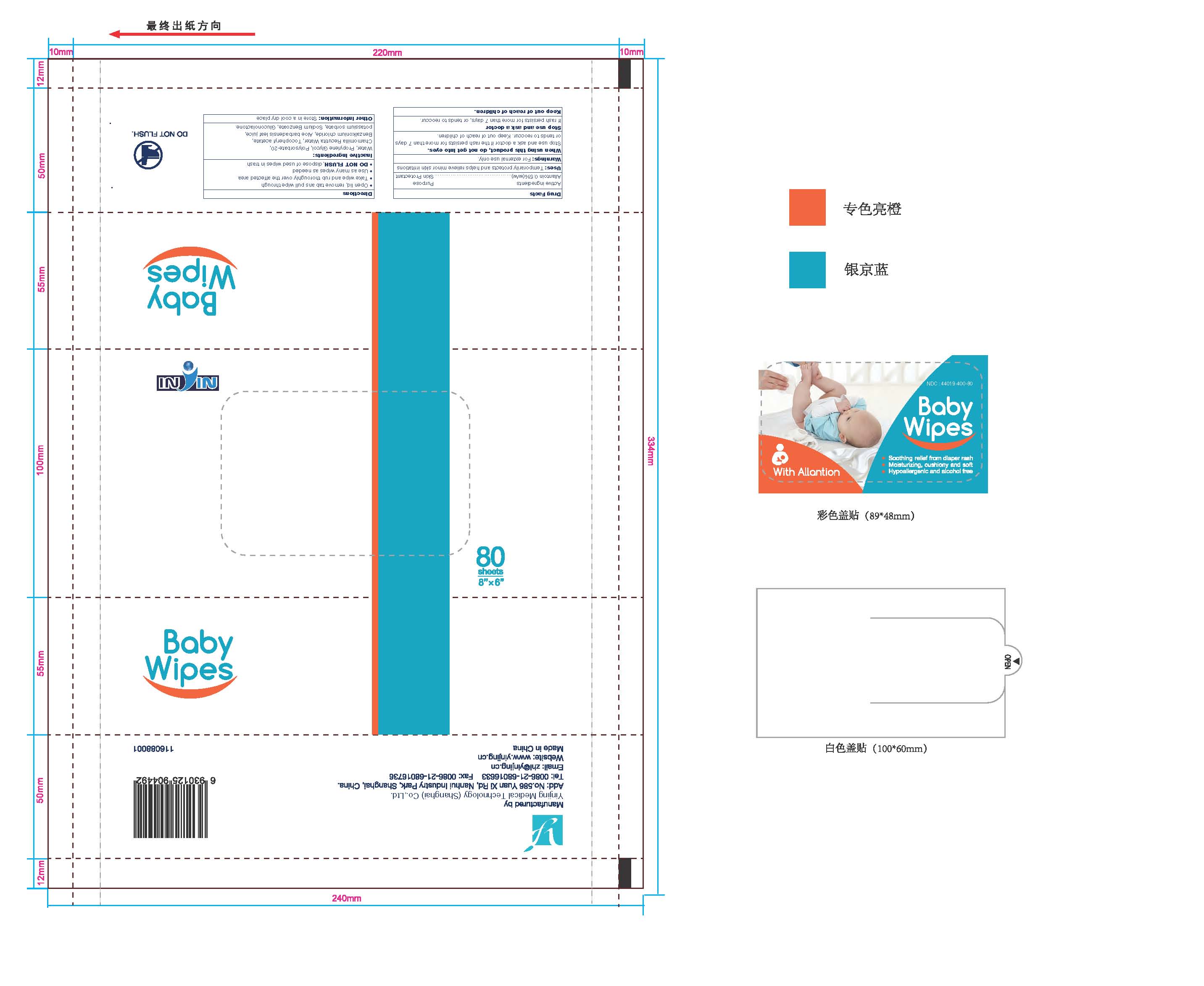 DRUG LABEL: Baby Wipes with Allantoin
NDC: 44019-400 | Form: LIQUID
Manufacturer: Yinjing Medical Technology (Shanghai) Co., Ltd.
Category: otc | Type: HUMAN OTC DRUG LABEL
Date: 20171227

ACTIVE INGREDIENTS: ALLANTOIN 0.5 g/100 g
INACTIVE INGREDIENTS: WATER; PROPYLENE GLYCOL; POLYSORBATE 20; .ALPHA.-TOCOPHEROL ACETATE; BENZALKONIUM CHLORIDE; ALOE VERA LEAF; POTASSIUM SORBATE; SODIUM BENZOATE; GLUCONOLACTONE

Baby Wipes with Allantoin

ACTIVE INGREDIENT

Allantoin 0.5%(w/w)

PURPOSE

Skin Protectant

Uses:

Temporarily protects and helps relieve minor skin irritations

Warnings:

For external use only.

When using this product, do not get into eyes.

Stop use and ask a doctor if the rash persists for more than 7 days,
or tends to reoccur. Keep out of reach of children

Stop use and ask a doctor

if rash persists for more than 7 days, or tends to reoccur.

Directions

- Open lid, remove tab ans pull wipe through
- Take wipe and rub thoroughly over the affected area
- Use as many wipes as needed
- DO NOT FLUSH,dispose of used wipes in trash

Inactive Ingredients:

Water, Propylene Glycol, Polysorbate-20, Chamomilla Recutita Water, Tocopheryl acetate, Benzalkonium chloride, Aloe barbadensis leaf juice, potassium sorbate, Sodium Benzoate, Gluconolactone.

Other Information:

Store in a cool dry place